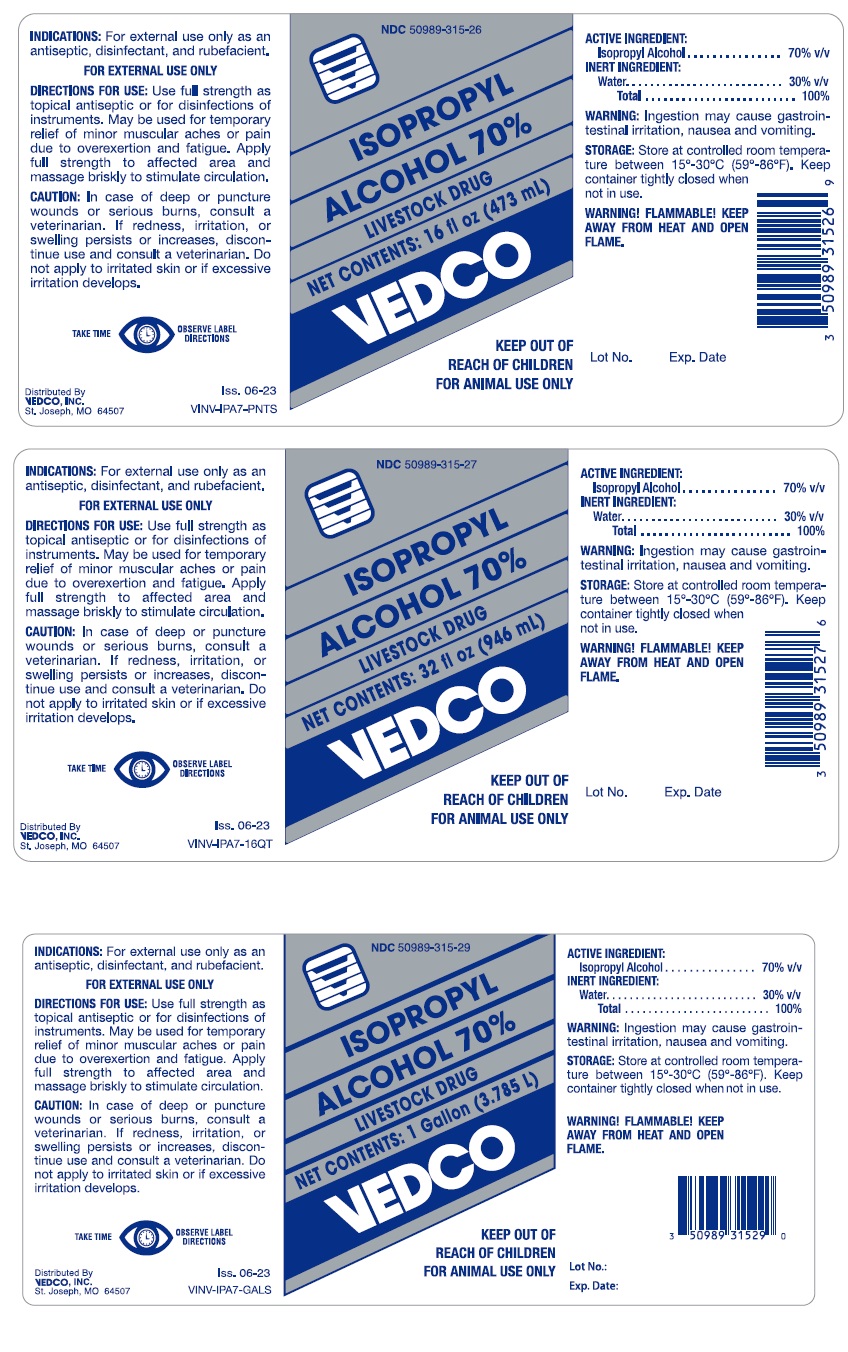 DRUG LABEL: ISOPROPYL ALCOHOL
NDC: 50989-315 | Form: LIQUID
Manufacturer: Vedco, Inc.
Category: animal | Type: OTC ANIMAL DRUG LABEL
Date: 20250514

ACTIVE INGREDIENTS: ISOPROPYL ALCOHOL 70 L/100 L
INACTIVE INGREDIENTS: WATER 30 L/100 L

WARNINGS AND PRECAUTIONS

ISOPROPYL ALCOHOL 70%

LIVESTOCK DRUG

NET CONTENTS:

16 fl oz (473 mL)/32 fl oz (960 mL)/1 Gallon (3.785 L)

KEEP OUT OF REACH OF CHILDREN.

FOR ANIMAL USE ONLY.

INDICATIONS: For external use only as an antiseptic, disinfectant, and rubefacient.

FOR EXTERNAL USE ONLY

DIRECTIONS FOR USE: Use full strength as topical antiseptic or for disinfections of instruments. May be used for temporary relief of minor muscular aches or pain due to overexertion and fatigue. Apply full strength to affected area and massage briskly to stimulate circulation.

CAUTION: In case of deep or puncture wounds or serious burns, consult a veterinarian. If redness, irritation, or swelling persists or increases, discontinue use and consult a veterinarian. Do not apply to irritated skin or if excessive irritation develops.

ACTIVE INGREDIENT:

Isopropyl Alcohol ................. 70% v/v

INERT INGREDIENT:

Water ...................................30% v/v

Total......................................100%

WARNING: Ingestion may cause gastrointestinal irritation, nausea and vomiting.

STORGE: Store at controlled room temperature between 15º-30ºC (59º-86ºF). Keep container tightly closed when not in use.

WARNING! FLAMMABLE! KEEP AWAY FROM HEAT AND OPEN FLAME.

Distributed By

VEDCO, INC.

St. Joseph, MO 64507